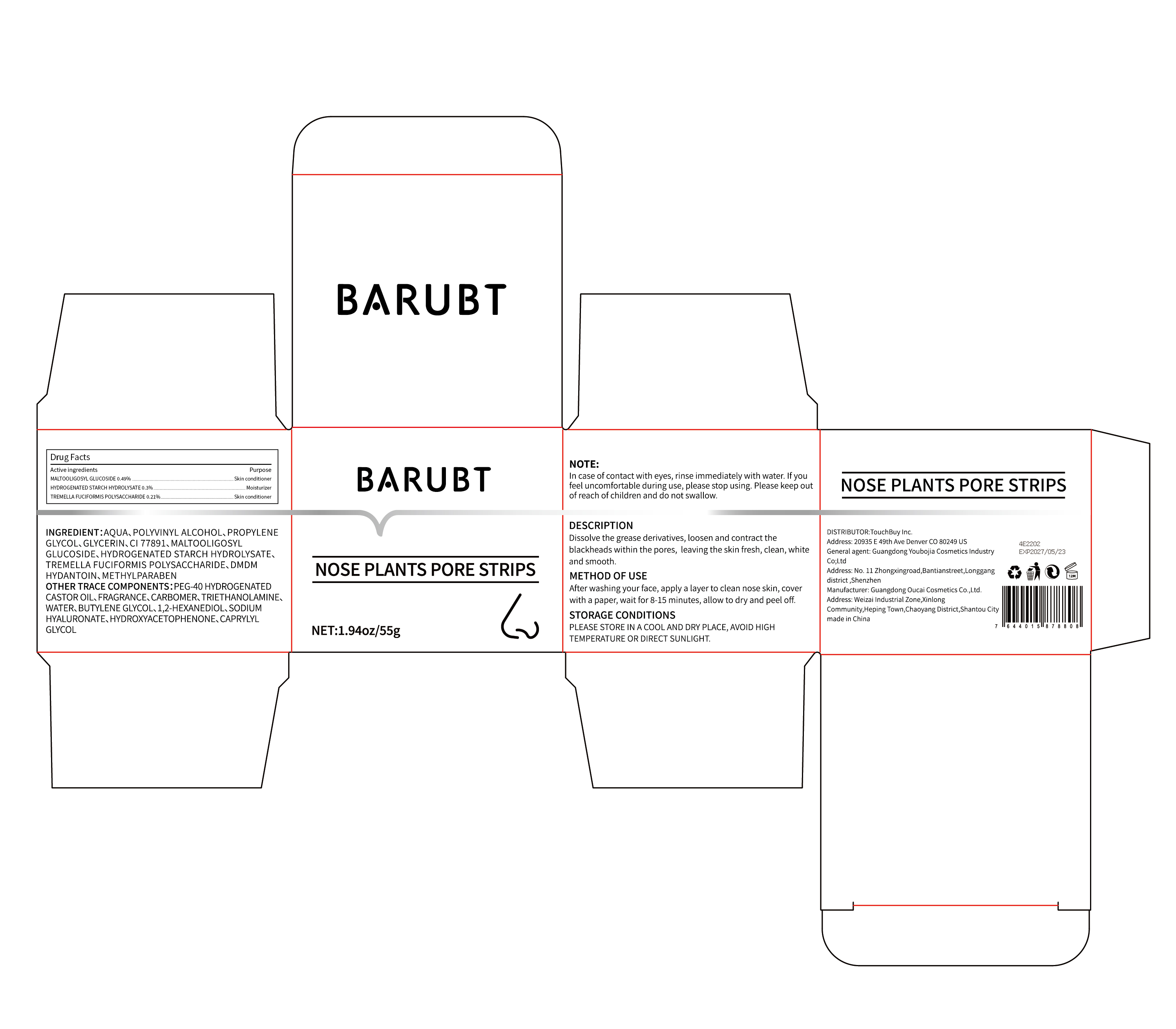 DRUG LABEL: BARUBT NOSE PLANTS PORE STRIPS
NDC: 84712-003 | Form: CREAM
Manufacturer: Guangdong Youbaijia Cosmetic Industry Co., Ltd
Category: otc | Type: HUMAN OTC DRUG LABEL
Date: 20240908

ACTIVE INGREDIENTS: MALTOOLIGOSYL GLUCOSIDE 0.27 g/55 g; HYDROGENATED STARCH HYDROLYSATE 0.165 g/55 g
INACTIVE INGREDIENTS: GLYCERIN 1.1 g/55 g

ACTIVE INGREDIENT

MALTOOLIGOSYL GLUCOSIDE 0.49%
HYDROGENATED STARCH HYDROLYSATE 0.3%
TREMELLA FUCIFORMIS POLYSACCHARIDE 0.12%

PURPOSE

Dissolve the grease derivatives, loosen and contract the blackheads within the pores, leaving the skin fresh, clean, white and smooth.

INDICATIONS AND USAGE

After washing your face, apply a layer to clean nose ski, cover with a paper, wait for 8-15 minutes, allow to dry and peel off.

WARNINGS

For external use only

DO NOT USE

on damaged or broken skin

STOP USE

If you feel uncomfortable during use, please stop using.

KEEP OUT OF REACH OF CHILDREN

Please keep out of reach of children and do not swallow.

WHEN USING

In case of contact with eyes, rinse immediately with water.

QUESTIONS

Company phone number: +1 818 579 7288
Company e-mail: jessie@registeragentllc.com

STORAGE AND HANDLING

PLEASE STORE IN A COOL AND DRY PLACE, AVOID HIGH TEMPERATURE OR DIRECT SUNLIGHT.

INACTIVE INGREDIENT

AQUA
POLYVINYL ALCOHOL
PROPYLENE GLYCOL
GLYCERIN
CI77891
DMDM HYDANTOIN
METHYLPARABEN
PEG-40 HYDROGENATED CASTOR OIL
FRAGRANCE
CARBOMER
TRIETHANOLAMINE
WATER
BUTYLENE GLYCOL
1,2-HEXANEDIOL
SODIUM HYALURONATE
HYDROXYACETOPHENONE
CAPRYLYL GLYCOL

DOSAGE AND ADMINISTRATION

METHOD OF USE

- washing your face
- apply a layer to clean nose skin
- coverwith a paper, wait for 8-15 minutes
- allow to dry and peel off.